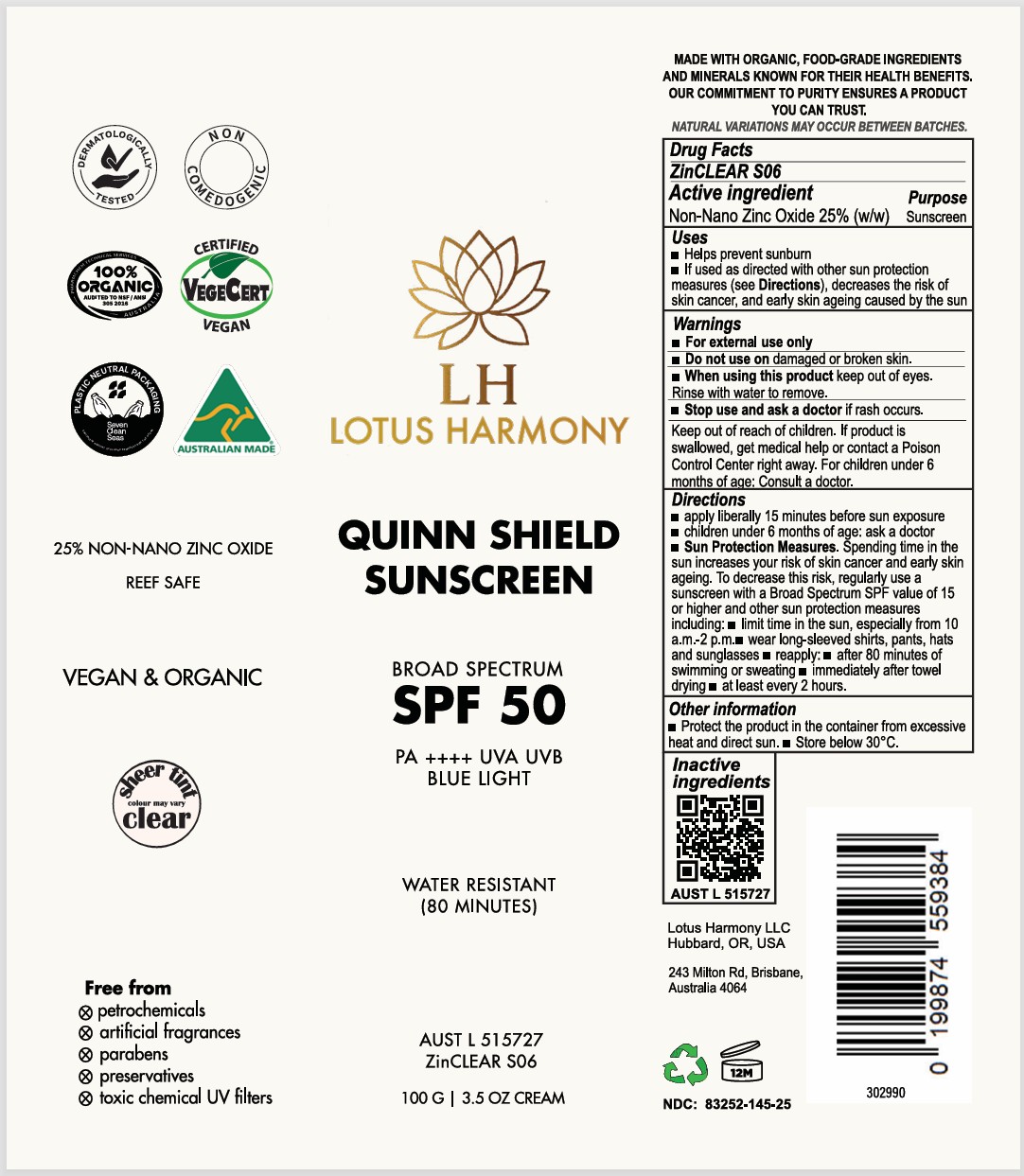 DRUG LABEL: Lotus Harmony - Quinn Shield Sunscreen SPF50
NDC: 83252-145 | Form: CREAM
Manufacturer: VEGANIC SKN LIMITED
Category: otc | Type: HUMAN OTC DRUG LABEL
Date: 20260215

ACTIVE INGREDIENTS: ZINC OXIDE 25 kg/100 kg
INACTIVE INGREDIENTS: COCO-CAPRYLATE/CAPRATE; SODIUM CHLORIDE; POLYGLYCERYL-3 RICINOLEATE; XANTHAN GUM; FERRIC OXIDE RED; FERRIC OXIDE YELLOW; FERROSOFERRIC OXIDE; COCONUT ALKANES; HELIANTHUS ANNUUS (SUNFLOWER) SEED OIL; ALPHA-TOCOPHEROL ACETATE; WATER; POLYHYDROXYSTEARIC ACID (2300 MW); ISOSTEARIC ACID; CANDELILLA WAX; GLYCERYL STEARATE CITRATE

Lotus Harmony - Quinn Shield Sunscreen SPF50

ACTIVE INGREDIENT

Zinc oxide - 25%

PURPOSE

Sunscreen

INDICATIONS AND USAGE

kindly refer to label picture

WARNINGS

For external use only.

Do not use on damaged r broken skin.

When using this product keep out of eyes. Rinse with water to remove.
Stop use and ask a doctor if rash occurs.

Keep out of reach of children.

If product is swallowed, get medical help or contact a Poison Control Center right away.

Keep out of reach of children.

DOSAGE AND ADMINISTRATION

Kindly refer to Label

INACTIVE INGREDIENT

See ingredients on label